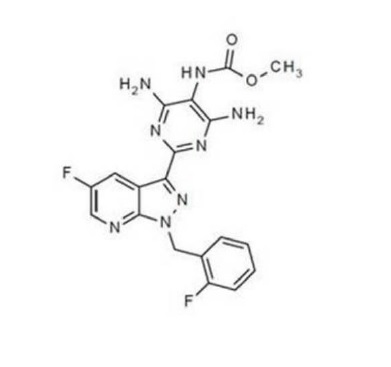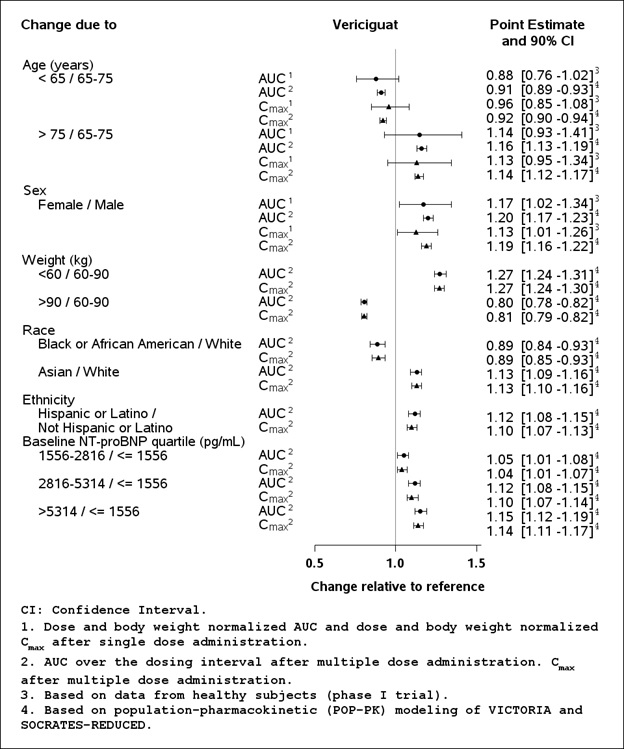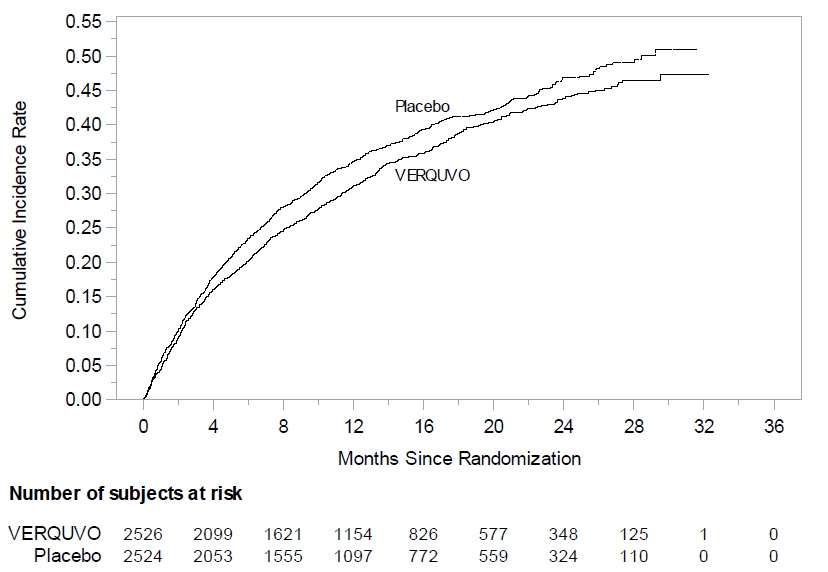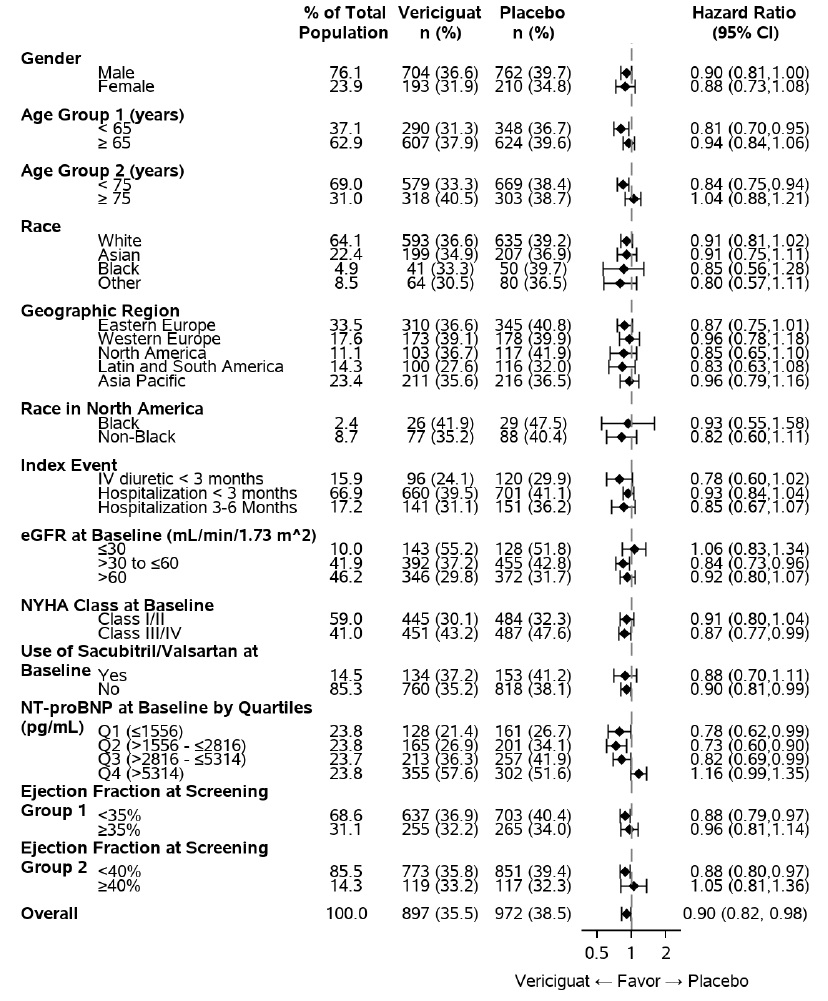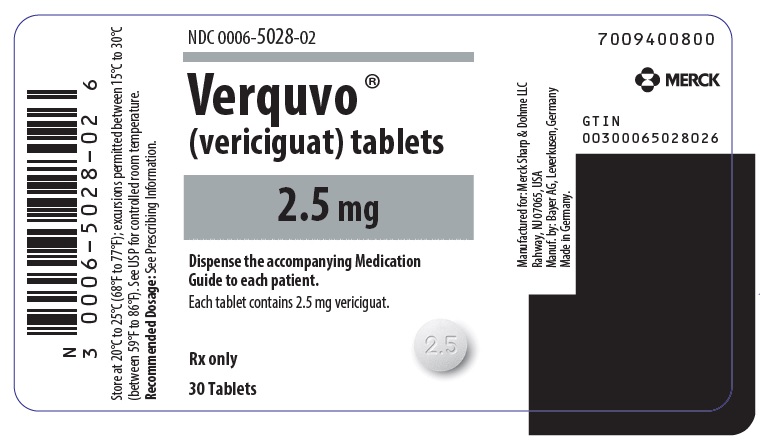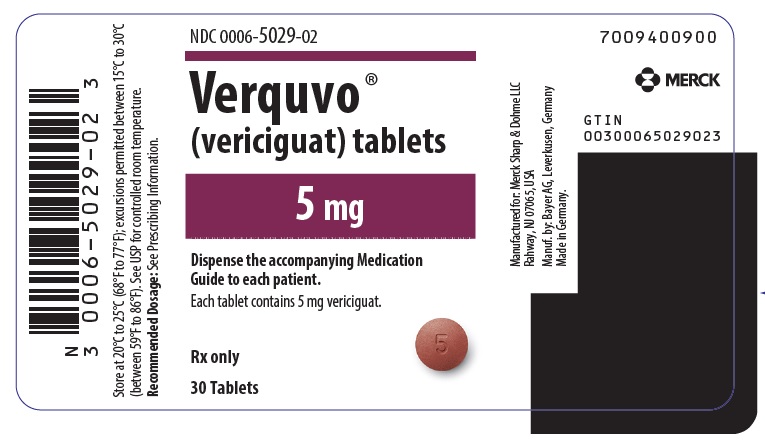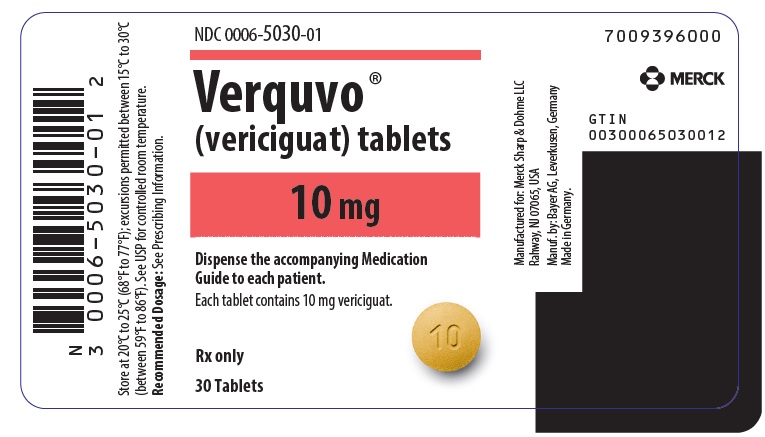 DRUG LABEL: VERQUVO
NDC: 0006-5028 | Form: TABLET, FILM COATED
Manufacturer: Merck Sharp & Dohme LLC
Category: prescription | Type: HUMAN PRESCRIPTION DRUG LABEL
Date: 20260121

ACTIVE INGREDIENTS: VERICIGUAT 2.5 mg/1 1
INACTIVE INGREDIENTS: MICROCRYSTALLINE CELLULOSE; CROSCARMELLOSE SODIUM; HYPROMELLOSE 2910 (5 MPA.S); LACTOSE MONOHYDRATE; MAGNESIUM STEARATE; SODIUM LAURYL SULFATE; TALC; TITANIUM DIOXIDE

HIGHLIGHTS OF PRESCRIBING INFORMATION

These highlights do not include all the information needed to use VERQUVO safely and effectively. See full prescribing information for VERQUVO.
VERQUVO ® (vericiguat) tablets, for oral use
Initial U.S. Approval: 2021

RECENT MAJOR CHANGES

Dosage and Administration (2.1) | 01/2026

WARNING: EMBRYO-FETAL TOXICITY

See full prescribing information for complete boxed warning.

- Do not administer VERQUVO to a pregnant female because it may cause fetal harm. (4, 5.1, 8.1)
- Females of reproductive potential: Exclude pregnancy before the start of treatment. To prevent pregnancy, females of reproductive potential must use effective forms of contraception during treatment and for one month after stopping treatment. (2.2, 5.1, 8.3)

1 INDICATIONS AND USAGE

VERQUVO is a soluble guanylate cyclase (sGC) stimulator, indicated to reduce the risk of cardiovascular death and heart failure (HF) hospitalization following a hospitalization for heart failure or need for outpatient IV diuretics, in adults with symptomatic chronic HF and ejection fraction less than 45%. (1)

2 DOSAGE AND ADMINISTRATION

- The recommended starting dose of VERQUVO is 5 mg orally once daily with food. (2.1)
- For patients at risk of symptomatic hypotension, the recommended starting dose is 2.5 mg orally once daily with food. (2.1)
- Double the dose after approximately every 2 weeks to reach the target maintenance dose of 10 mg once daily, as tolerated by the patient. (2.1)
- Tablets may be crushed and mixed with water for patients unable to swallow whole tablets. (2.1)

3 DOSAGE FORMS AND STRENGTHS

Tablets: 2.5 mg, 5 mg and 10 mg (3)

4 CONTRAINDICATIONS

- Patients with concomitant use of other soluble guanylate cyclase (sGC) stimulators. (4, 7.1)
- Pregnancy (4)

6 ADVERSE REACTIONS

Most common adverse reactions reported in ≥5% are hypotension and anemia. (6.1)

To report SUSPECTED ADVERSE REACTIONS, contact Merck Sharp & Dohme LLC at 1-877-888-4231 or FDA at 1-800-FDA-1088 or www.fda.gov/medwatch.

7 DRUG INTERACTIONS

- PDE-5 Inhibitors: Concomitant use is not recommended. (7.2)

8 USE IN SPECIFIC POPULATIONS

- Lactation: Breastfeeding is not recommended (8.2)

FULL PRESCRIBING INFORMATION

WARNING: EMBRYO-FETAL TOXICITY

Females of reproductive potential: Exclude pregnancy before the start of treatment. To prevent pregnancy, females of reproductive potential must use effective forms of contraception during treatment and for one month after stopping treatment. Do not administer VERQUVO to a pregnant female because it may cause fetal harm [see Dosage and Administration (2.2), Warnings and Precautions (5.1), and Use in Specific Populations (8.3)].

1 INDICATIONS AND USAGE

VERQUVO® is indicated to reduce the risk of cardiovascular death and heart failure (HF) hospitalization following a hospitalization for heart failure or need for outpatient IV diuretics, in adults with symptomatic chronic HF and ejection fraction less than 45% [see Clinical Studies (14)].

2 DOSAGE AND ADMINISTRATION

2.1 Recommended Dosage

The recommended starting dose of VERQUVO is 5 mg orally once daily with food.

For patients at risk of symptomatic hypotension, the recommended starting dose is 2.5 mg orally once daily with food [see Clinical Trials Experience (6.1)].

Double the dose approximately every 2 weeks to reach the target maintenance dose of 10 mg once daily, as tolerated by the patient.

For patients who are unable to swallow whole tablets, VERQUVO may be crushed and mixed with water immediately before administration [see Clinical Pharmacology (12.3)].

2.2 Pregnancy Testing in Females of Reproductive Potential

Obtain a pregnancy test in females of reproductive potential prior to initiating treatment with VERQUVO [see Warnings and Precautions (5.1) and Use in Specific Populations (8.3)].

3 DOSAGE FORMS AND STRENGTHS

- VERQUVO 2.5 mg (vericiguat 2.5 mg) are round, biconvex, white film-coated tablets debossed with “2.5” on one side and “VC” on the other side.
- VERQUVO 5 mg (vericiguat 5 mg) are round, biconvex, brown-red film-coated tablets debossed with “5” on one side and “VC” on the other side.
- VERQUVO 10 mg (vericiguat 10 mg) are round, biconvex, yellow-orange film-coated tablets debossed with “10” on one side and “VC” on the other side.

4 CONTRAINDICATIONS

VERQUVO is contraindicated in patients with concomitant use of other soluble guanylate cyclase (sGC) stimulators [see Drug Interactions (7.1)].

VERQUVO is contraindicated in pregnancy [see Warnings and Precautions (5.1) and Use in Specific Populations (8.1)].

5 WARNINGS AND PRECAUTIONS

5.1 Embryo-Fetal Toxicity

Based on data from animal reproduction studies, VERQUVO may cause fetal harm when administered to a pregnant woman. Advise females of reproductive potential of the potential risk to a fetus. Obtain a pregnancy test before the start of treatment. Advise females of reproductive potential to use effective contraception during treatment with VERQUVO and for at least one month after the final dose [see Dosage and Administration (2.2) and Use in Specific Populations (8.1, 8.3)].

6 ADVERSE REACTIONS

6.1 Clinical Trials Experience

Because clinical trials are conducted under widely varying conditions, adverse reaction rates observed in the clinical trials of a drug cannot be directly compared to rates in the clinical trials of another drug and may not reflect the rates observed in practice.

VERQUVO was evaluated in VICTORIA, which included 2,519 patients treated with VERQUVO (up to 10 mg once daily). The mean duration of VERQUVO exposure was 1 year, and the maximum duration was 2.6 years [see Clinical Studies (14)]. Table 1 lists adverse drug reactions occurring more commonly with VERQUVO than placebo and in ≥5% of patients treated with VERQUVO in VICTORIA.

Table 1: Adverse Drug Reactions Occurring with VERQUVO in VICTORIA
Adverse Drug Reaction | VERQUVO % N = 2,519 | Placebo % N = 2,515
Hypotension | 16 | 15
Anemia | 10 | 7

VELOCITY

The safety and tolerability of VERQUVO 5 mg once daily as a starting dose was evaluated in VELOCITY, a single-arm, open-label, 2-week study in 106 patients with symptomatic chronic heart failure (NYHA class II–IV) and left ventricular ejection fraction < 45%. Patients were excluded from the study if they experienced symptomatic hypotension within 4 weeks before screening. Treatment initiation with VERQUVO 5 mg once daily in VELOCITY was similarly tolerated as treatment initiation of 2.5 mg once daily in the VICTORIA study.

7 DRUG INTERACTIONS

7.1 Other Soluble Guanylate Cyclase Stimulators

VERQUVO is contraindicated in patients with concomitant use of other soluble guanylate cyclase (sGC) stimulators [see Contraindications (4)].

7.2 PDE-5 Inhibitors

Concomitant use of VERQUVO with PDE-5 inhibitors is not recommended because of the potential for hypotension [see Clinical Pharmacology (12.2)].

8 USE IN SPECIFIC POPULATIONS

8.1 Pregnancy

Pregnancy Surveillance Program

There is a Pregnancy Surveillance Program that monitors pregnancy outcomes in women exposed to VERQUVO during pregnancy. Health care providers should report any prenatal exposure to VERQUVO by calling 1-877-888-4231 or at https://pregnancyreporting.verquvo-us.com.

Risk Summary

Based on data from animal reproduction studies, VERQUVO may cause fetal harm when administered to a pregnant woman and is contraindicated during pregnancy [see Contraindications (4)]. There are no available data with VERQUVO use in pregnant women. In animal reproduction studies, oral administration of vericiguat to pregnant rabbits during organogenesis, at ≥4 times the human exposure (total AUC) with the maximum recommended human dose (MRHD) of 10 mg, resulted in malformations of the heart and major vessels, as well as increased number of abortions and resorptions (see Animal Data). In a pre/postnatal toxicity study, vericiguat administered orally to rats during gestation through lactation caused maternal toxicity, which resulted in decreased pup body weight gain (≥10 times the MRHD) and increased pup mortality (24 times the MRHD) during the preweaning period (see Animal Data).

The estimated background risk of major birth defects and miscarriage for the indicated population is unknown. All pregnancies have a background risk of birth defect, loss, or other adverse outcomes. In the U.S. general population, the estimated background risk of major birth defects and miscarriage in clinically recognized pregnancies is 2-4% and 15-20%, respectively.

Data

Animal Data

In an embryo-fetal development study in rabbits, vericiguat was administered orally to pregnant rabbits during the period of organogenesis from gestation day (GD) 6 to 20 at doses of 0.75, 2.5 or 7.5 mg/kg/day. An increased incidence of cardiac ventricular septal defect along with truncus arteriosus communis was observed at ≥2.5 mg/kg/day, which is ≥4 times the human exposure at the MRHD. Maternal toxicity (decreased food consumption and body weight loss), which may have resulted in late spontaneous abortions and resorptions was noted at ≥2.5 mg/kg/day (≥4 times the human exposure at the MRHD). There were no maternal toxicity or abortions/resorptions and no malformations of the heart and major vessels in rabbits at an exposure approximately equivalent to the human exposure at the MRHD.

In a prenatal developmental toxicity study in rats, vericiguat was administered orally to pregnant rats during the period of organogenesis from GD 6 to 17 at doses of 5, 15 or 50 mg/kg/day. No developmental toxicity was observed up to the highest dose (36 times the human exposure [total AUC] at the MRHD). Maternal toxicity (decreased body weight gain and food consumption) was observed at ≥15 mg/kg/day (≥10 times the human exposure at the MRHD). There was no maternal toxicity at 5 mg/kg/day (4 times the human exposure at the MRHD).

In a pre-postnatal development study in rats, vericiguat was administered orally at doses of 7.5, 15 or 30 mg/kg/day from GD 6 through lactation day 21. Maternal toxicity (decreases in food consumption and body weight gain) was observed at all dose levels ≥6 times the human exposure (total AUC) at the MRHD and resulted in decreased pup body weight gain at ≥15 mg/kg/day (≥10 times the human exposure at the MRHD) and pup mortality at 30 mg/kg/day (24 times the MRHD).

[^14C]-vericiguat was administered orally to pregnant rats at a dose of 3 mg/kg. Vericiguat-related material was transferred across the placenta, with fetal plasma concentrations of approximately 67% maternal concentrations on GD 19.

8.2 Lactation

Risk Summary

There are no data on the presence of vericiguat in human milk, the effects on the breastfed infant, or the effects on milk production. Vericiguat is present in the milk of lactating rats and it is likely that vericiguat or its metabolites are present in human milk (see Data). Because of the potential for serious adverse reactions in breastfed infants from VERQUVO, advise women not to breastfeed during treatment with VERQUVO.

Data

[^14C]-vericiguat was administered intravenously to lactating rats at a dose of 1 mg/kg. Vericiguat-related material was excreted into milk at concentrations approximately 12% maternal plasma concentrations on LD 8.

8.3 Females and Males of Reproductive Potential

Pregnancy Testing

Verify the pregnancy status in females of reproductive potential prior to initiating VERQUVO [see Dosage and Administration (2.2), Warnings and Precautions (5.1) and Use in Specific Populations (8.1)].

Contraception

Females

VERQUVO may cause fetal harm when administered to a pregnant woman. Advise females of reproductive potential to use effective contraception during treatment and for one month after the final dose [see Warnings and Precautions (5.1)].

8.4 Pediatric Use

Safety and effectiveness of VERQUVO have not been established in pediatric patients.

8.5 Geriatric Use

No dosage adjustment of VERQUVO is required in geriatric patients. In VICTORIA, a total of 1,596 (63%) patients treated with VERQUVO were 65 years and older, and 783 (31%) patients treated with VERQUVO were 75 years and older. No overall differences in safety or efficacy of VERQUVO were observed between patients aged 65 years and older compared to younger patients, but greater sensitivity of some older individuals cannot be ruled out [see Clinical Pharmacology (12.3) and Clinical Studies (14)].

8.6 Renal Impairment

No dosage adjustment of VERQUVO is recommended in patients with estimated glomerular filtration rate (eGFR) ≥15 mL/min/1.73m^2 who are not on dialysis. VERQUVO has not been studied in patients with eGFR <15 mL/min/1.73m^2 at treatment initiation or on dialysis [see Clinical Pharmacology (12.3) and Clinical Studies (14)].

8.7 Hepatic Impairment

No dosage adjustment of VERQUVO is recommended in patients with mild or moderate hepatic impairment (e.g., Child-Pugh A or B). VERQUVO has not been studied in patients with severe hepatic impairment (e.g., Child-Pugh C) [see Clinical Pharmacology (12.3)].

10 OVERDOSAGE

Limited data are available with regard to overdosage in human patients treated with VERQUVO. In VICTORIA, doses up to 10 mg have been studied. In a study of patients with preserved ejection fraction heart failure (left ventricular ejection fraction ≥45%), multiple doses of VERQUVO 15 mg have been studied and were generally well tolerated. In the event of an overdose, hypotension may result. Symptomatic treatment should be provided. VERQUVO is unlikely to be removed by hemodialysis because of high protein binding.

11 DESCRIPTION

VERQUVO tablets contains vericiguat, a soluble guanylate cyclase stimulator.

The chemical name of vericiguat is methyl {4,6-diamino-2-[5-fluoro-1-(2-fluorobenzyl)-1H-pyrazolo[3,4-b] pyridin-3-yl] pyrimidin-5-yl} carbamate. The molecular formula is C19H16F2N8O2 and the molecular weight is 426.39 g/mol.

The chemical structure is:

Vericiguat is a white to yellowish powder that is freely soluble in dimethyl sulfoxide; slightly soluble in acetone; very slightly soluble in ethanol, acetonitrile, methanol, and ethyl acetate; and practically insoluble in 2-propanol.

VERQUVO® is available as film-coated tablets for oral administration, containing 2.5 mg of vericiguat, 5 mg of vericiguat or 10 mg of vericiguat.
The tablet inactive ingredients are croscarmellose sodium, hypromellose, lactose monohydrate, magnesium stearate, microcrystalline cellulose, and sodium lauryl sulfate.

The film coating contains hypromellose, talc and titanium dioxide. The film coating for the 5 mg of VERQUVO tablet also contains ferric oxide red. The film coating for the 10 mg of VERQUVO tablet also contains ferric oxide yellow.

12 CLINICAL PHARMACOLOGY

12.1 Mechanism of Action

Vericiguat is a stimulator of soluble guanylate cyclase (sGC), an important enzyme in the nitric oxide (NO) signaling pathway. When NO binds to sGC, the enzyme catalyzes the synthesis of intracellular cyclic guanosine monophosphate (cGMP), a second messenger that plays a role in the regulation of vascular tone, cardiac contractility, and cardiac remodeling. Heart failure is associated with impaired synthesis of NO and decreased activity of sGC, which may contribute to myocardial and vascular dysfunction. By directly stimulating sGC, independently of and synergistically with NO, vericiguat augments levels of intracellular cGMP, leading to smooth muscle relaxation and vasodilation.

12.2 Pharmacodynamics

The mean reduction in systolic blood pressure was approximately 1 to 2 mm Hg greater in patients who received VERQUVO compared with placebo.

VERQUVO demonstrated a dose-dependent reduction in NT-proBNP, a biomarker in heart failure, at 12 weeks compared to placebo when added to standard of care. The estimated reduction from baseline NT-proBNP at week 32 was greater in patients who received VERQUVO compared with placebo [see Clinical Studies (14)].

Cardiac Electrophysiology
There was no evidence of proarrhythmic risk in an in vitro assessment of vericiguat or its major N-glucuronide metabolite. No inhibition of cardiac ion channels (hERG, hNav1.5, or hKvLQT1/mink) was observed at substantial multiples of their unbound Cmax values at the recommended target dose of 10 mg.

The integrated risk assessment of nonclinical and clinical data supports that administration of vericiguat 10 mg is not associated with clinically meaningful QTc prolongation.

Drug Interaction Studies
No clinically significant differences on bleeding time or platelet aggregation were observed when a single dose of vericiguat 15 mg was used concomitantly with 500 mg of aspirin.

No clinically significant differences in prothrombin time or the activities of Factors II, VII, and X were observed when multiple doses of VERQUVO 10 mg once daily were used concomitantly with a single dose of warfarin 25 mg.

No clinically significant differences on seated blood pressure (BP) were observed when multiple doses of VERQUVO 2.5 mg were used concomitantly with sacubitril/valsartan in healthy subjects.

No clinically significant differences on seated BP were observed when multiple doses of VERQUVO 10 mg were used concomitantly with short- and long-acting nitrates (nitroglycerin spray and isosorbide mononitrate [ISMN] modified release 60 mg) in patients with coronary artery disease. In patients with heart failure, concomitant use with short-acting nitrates was well tolerated, but there is limited experience with long-acting nitrates.

Concomitant use of VERQUVO 10 mg with single doses of sildenafil (25, 50, or 100 mg) was associated with additional seated BP reduction of up to 5.4 mm Hg (systolic/diastolic BP, MAP), compared to administration of VERQUVO alone. There is limited experience with concomitant use of VERQUVO and PDE-5 inhibitors in patients with heart failure.

12.3 Pharmacokinetics

Vericiguat steady-state mean (coefficient of variation %) Cmax is 350 mcg/L (29%) and AUC is 6,680 mcg•h/L (33.9%) following administration of VERQUVO 10 mg in patients with heart failure. Vericiguat pharmacokinetics increases in a slightly less than dose-proportional manner. Vericiguat accumulates in plasma up to 155-171% and reaches steady-state after approximately 6 days.

Absorption
The absolute bioavailability of vericiguat is 93% when taken with food. Results were comparable when VERQUVO was administered orally as a whole tablet or as a crushed tablet in water.

Effect of Food
Administration of VERQUVO 10 mg with a high-fat, high-calorie meal increases Tmax from about 1 hour (fasted) to about 4 hours (fed), reduces PK variability, and increases vericiguat AUC by 44% and Cmax by 41% compared with administration in the fasted state. Similar results were obtained when VERQUVO was administered with a low-fat, low-calorie meal when compared to administration with a high-fat, high-calorie meal.

Distribution
The mean steady-state volume of distribution of vericiguat is approximately 44 L in healthy subjects. Protein binding (primarily to serum albumin) of vericiguat is about 98%.

Elimination
The half-life of vericiguat is 30 hours in patients with heart failure. Clearance in healthy subjects is 1.6 L/h.

Metabolism
Vericiguat primarily undergoes glucuronidation by UGT1A9 and to a lesser extent, by UGT1A1 to form an inactive N-glucuronide metabolite. CYP-mediated metabolism is a minor clearance pathway (<5%).

Excretion
Following oral administration of radiolabeled vericiguat to healthy subjects, approximately 53% of the dose was excreted in urine (primarily as inactive metabolite) and 45% in feces (primarily as unchanged drug).

Specific Populations
Renal Impairment
In patients with heart failure with mild, moderate, and severe renal impairment not requiring dialysis, the mean exposure (AUC) of vericiguat was increased by 5%, 13%, and 20% respectively, compared to patients with normal renal function. These differences in exposure are not considered clinically relevant. The pharmacokinetics of vericiguat have not been studied in patients with eGFR <15 mL/min/1.73m^2 at treatment initiation or on dialysis [see Use in Specific Populations (8.6)].

In a dedicated clinical pharmacology study, otherwise healthy participants with mild, moderate, and severe renal impairment, had 8%, 73%, and 143% respectively, higher mean vericiguat exposure (unbound AUC normalized for body weight) after a single dose compared to healthy controls.

The apparent discrepancy of the effect of renal impairment on vericiguat exposure between the dedicated clinical pharmacology study and the analysis in patients with heart failure may be attributed to differences in study design and size.

Hepatic Impairment
No clinically relevant increases in exposure (unbound AUC normalized for body weight) were observed for individuals with mild and moderate hepatic impairment (Child Pugh A-B). Mean vericiguat exposures were 21% and 47% higher, respectively, compared to individuals with normal hepatic function. The pharmacokinetics of vericiguat have not been studied in patients with severe hepatic impairment (e.g., Child-Pugh C) [see Use in Specific Populations (8.7)].

No clinically significant differences in the pharmacokinetics of vericiguat were observed based on age, sex, race/ethnicity (Black, White, Asian, Hispanic, Latino), body weight, or baseline NT-proBNP. Effects of specific populations on the pharmacokinetics of vericiguat are shown in Figure 1.

Figure 1: Pharmacokinetics of Vericiguat in Specific Populations

Drug Interaction Studies
Clinical Studies
Effects of Other Drugs on the Pharmacokinetics of Vericiguat
Vericiguat is less soluble at neutral than at acidic pH. Pre- and co-treatment with drugs that increase gastric pH, such as proton pump inhibitors or antacids, decrease vericiguat exposure (AUC) by about 30% following fasted administration. However, co-treatment with drugs that increase gastric pH did not affect vericiguat exposure in patients with heart failure when vericiguat was taken as directed with food.

No clinically significant differences on vericiguat pharmacokinetics were observed with co-administration of mefenamic acid (UGT1A9 inhibitor), ketoconazole (multi-pathway CYP and transporter inhibitor), rifampin (inducer), digoxin (P-gp substrate), warfarin, aspirin, sildenafil, or the combination of sacubitril/valsartan in healthy subjects. No clinically significant differences on vericiguat pharmacokinetics were predicted with co-administration of atazanavir (UGT1A1 inhibitor).

Effects of Vericiguat on the Pharmacokinetics of Other Drugs
No clinically significant differences on the pharmacokinetics of midazolam (CYP3A substrate), digoxin (P-gp substrate), warfarin, sildenafil, or the combination of sacubitril (including metabolite LBQ657)/valsartan were observed when coadministered with VERQUVO in healthy subjects.

In Vitro Studies
Cytochrome P450 (CYP) enzymes: vericiguat is not an inhibitor of CYP1A2, 2B6, 2C8, 2C9, 2C19, or 2D6, 3A4 and is not an inducer of CYP1A2, 2B6, or 3A4.

Uridine diphosphate (UDP)-glucuronosyl transferase (UGT) enzymes: vericiguat is not an inhibitor of UGT1A1, 1A4, 1A6, 1A9, 2B4, or 2B7.

Transporter systems: vericiguat is a substrate of P-glycoprotein (P-gp) and breast cancer resistance protein (BCRP) but is not a substrate of organic cation transporter (OCT1) or organic anion transporting polypeptides (OATP1B1 and OATP1B3). Vericiguat is not an inhibitor of P-gp, BCRP, BSEP, OATP1B1/1B3, OAT1, OAT3, OCT1, OCT2, MATE1, or MATE2K.

13 NONCLINICAL TOXICOLOGY

13.1 Carcinogenesis, Mutagenesis, Impairment of Fertility

Carcinogenesis
Carcinogenicity was evaluated in 2-year studies conducted in CD1 mice and Wistar rats. Vericiguat did not show a carcinogenic effect in mice dosed up to 150 mg/kg/day (males) or up to 250 mg/kg/day (females). These doses were associated with exposures 41 times (males) or 78 (females) times the human exposure (total AUC) at the MRHD of 10 mg/day.

In the carcinogenicity study in rats, no vericiguat-related tumor or hyperplastic findings were observed at doses up to 20 mg/kg/day, at exposures of 16 (males) and 21 times (females) the human exposure at the MRHD.

Mutagenesis
Vericiguat was not genotoxic in the in vitro microbial mutagenicity (Ames) assay, the in vitro mouse lymphoma assay and the in vivo rat and mouse micronucleus assay.

Impairment of Fertility
There were no effects on fertility, mating performance or early embryonic development when vericiguat was administered to rats at up to 32 times the human exposure (total AUC) at the MRHD.

13.2 Animal Toxicology and/or Pharmacology

In growing rats, reversible effects on bone formation were observed, consisting of hypertrophy of growth plate and hyperostosis and remodeling of metaphyseal and diaphyseal bone. These effects were not observed after chronic administration of vericiguat at up to 22X (adult male rats), 25X (adult female rats), and 2.4X (adult dogs) the human exposure (total AUC) at the MRHD [see Use in Specific Populations (8.4)].

14 CLINICAL STUDIES

VICTORIA

VICTORIA was a randomized, parallel-group, placebo-controlled, double-blind, event-driven, multi-center trial comparing VERQUVO and placebo in 5,050 adult patients with symptomatic chronic heart failure (New York Heart Association [NYHA] class II-IV) and left ventricular ejection fraction (LVEF) less than 45% following a worsening heart failure event. A worsening heart failure event was defined as heart failure hospitalization within 6 months before randomization or use of outpatient IV diuretics for heart failure within 3 months before randomization.

Patients were randomized to receive VERQUVO 10 mg or matching placebo. VERQUVO was initiated at 2.5 mg once daily and increased at approximately 2 week intervals to 5 mg once daily and the target dose of 10 mg once daily, as tolerated. Placebo doses were similarly adjusted. After approximately 1 year, 90% of patients in both treatment groups were treated with the 10 mg target dose.

The primary endpoint was a composite of time to first event of CV death or hospitalization for heart failure. The median follow-up for the primary endpoint was 11 months.

The population was 64% Caucasian, 22% Asian, and 5% Black. The mean age was 67 years and 76% were male. At randomization, 59% of patients were NYHA Class II, 40% were NYHA Class III, and 1% were NYHA Class IV. The mean left ventricular ejection fraction (EF) was 29%. Approximately half of all patients had an EF <30%, and 14% had an EF between 40% and 45%. The most frequently reported medical history conditions other than heart failure included hypertension (79%), coronary artery disease (58%), hyperlipidemia (57%), diabetes mellitus (47%), atrial fibrillation (45%) and myocardial infarction (42%). At randomization, the mean eGFR was 62 mL/min/1.73 m^2; the majority of patients (88%) had an eGFR >30 mL/min/1.73 m^2. Sixty-seven percent of the patients were enrolled within 3 months of a HF-hospitalization index event; 17% were enrolled within 3 to 6 months of HF hospitalization, and 16% were enrolled within 3 months of outpatient treatment with IV diuretics for worsening HF. The median NT-proBNP level was 2800 pg/mL at randomization.

At baseline, 93% of patients were on a beta blocker, 73% of patients were on an angiotensin-converting enzyme (ACE) inhibitor or angiotensin II receptor blocker (ARB), 70% of patients were on a mineralocorticoid receptor antagonist (MRA), 15% of patients were on a combination of an angiotensin receptor and neprilysin inhibitor (ARNI), 28% of patients had an implantable cardiac defibrillator, and 15% had a biventricular pacemaker. Ninety-one percent of patients were treated with 2 or more heart failure medications (beta blocker, any renin-angiotensin system [RAS] inhibitor or MRA) and 60% of patients were treated with all 3. At baseline, 6% of patients were on ivabradine and 3% of patients were on a sodium glucose co-transporter 2 (SGLT2) inhibitor.

In VICTORIA, VERQUVO was superior to placebo in reducing the risk of CV death or heart failure hospitalization based on a time-to-event analysis (hazard ratio [HR]: 0.90, 95% confidence interval [CI], 0.82-0.98; p=0.019). Over the course of the study, there was a 4.2% annualized absolute risk reduction (ARR) with VERQUVO compared with placebo. The treatment effect reflected a reduction in both cardiovascular death and heart failure hospitalization (see Table 2).

Table 2: Treatment Effect for the Primary Composite Endpoint and the Secondary Endpoints of Cardiovascular Death and Heart Failure Hospitalization
 | VERQUVO N=2,526 |  | Placebo N=2,524 |  | Treatment Comparison
 | n (%) | Event rate: % of patients per year [Total patients with an event per 100 patient years at risk.] | n (%) | Event rate: % of patients per year | Hazard Ratio (95% CI) [Hazard ratio (VERQUVO over Placebo) and confidence interval from a Cox proportional hazards model.] | p-value [From the log-rank test.] | ARR [Absolute risk reduction, calculated as difference (Placebo-VERQUVO) in event rate per 100 patient years.]
Primary endpoint
Composite of; cardiovascular death; or heart failure; hospitalization [For patients with multiple events, only the first event contributing to the composite endpoint is counted.] | 897 (35.5) | 33.6 | 972 (38.5) | 37.8 | 0.90 (0.82, 0.98) | 0.019 | 4.2
Secondary endpoints
Cardiovascular death | 414 (16.4) | 12.9 | 441 (17.5) | 13.9 | 0.93 (0.81,1.06)
Heart failure; hospitalization | 691 (27.4) | 25.9 | 747 (29.6) | 29.1 | 0.90 (0.81,1.00)
N=Number of patients in Intent-to-Treat (ITT) population; n=Number of patients with an event.

The Kaplan-Meier curve (Figure 2) shows time to first occurrence of the primary composite endpoint of CV death or heart failure hospitalization.

Figure 2: Kaplan-Meier Curve for the Primary Composite Endpoint

A wide range of demographic characteristics, baseline disease characteristics, and baseline concomitant medications were examined for their influence on outcomes. The results of the prespecified subgroup analysis for the primary composite endpoint are shown in Figure 3.

Figure 3: Primary Composite Endpoint (CV Death or HF Hospitalization) – Subgroup Analysis

As shown above in Figure 3, the results of the primary composite endpoint were generally consistent across subgroups. However, among patients in the highest baseline NT-proBNP quartile, the estimated HRs for both CV death (HR: 1.16; 95% CI: [0.95, 1.43]) and first HF hospitalization (HR:1.19; 95%CI: [0.9,1.44]) were unfavorable, in contrast to the estimated HRs for patients in the three quartiles with lower NT-proBNP levels.

Secondary endpoints other than the components of the primary endpoint were tested according to a hierarchical testing procedure to control the family wise type I error rate. VERQUVO was superior to placebo in reducing the risk of total (first and recurrent) events of HF hospitalization and the first occurrence of either all-cause mortality or HF hospitalization (see Table 3).

Table 3: Treatment Effect for All-Cause Mortality or Heart Failure Hospitalization
 | VERQUVO N=2,526 |  | Placebo N=2,524 |  | Hazard Ratio (95% CI)
 | n (%) | Rate | n (%) | Rate | Hazard Ratio (95% CI)
Total events of heart; failure hospitalization | 1,223 | 38.3 [Event rate (total events, including recurrent events in the same patient, per 100 patient years at risk).] | 1,336 | 42.4 | 0.91 [Hazard ratio (VERQUVO over Placebo), based on an Andersen-Gill model.] (0.84, 0.99)
Composite of all-; cause mortality or; heart failure; hospitalization [For patients with multiple events, only the first event contributing to the composite endpoint is counted in this row and the applicable subsequent rows. Thus, any deaths occurring after a heart failure hospitalization are not counted.] | 957 (37.9) | 35.9 [Incidence rate (total patients with ≥1 event per 100 patient years at risk).] | 1,032 (40.9) | 40.1 | 0.90 [Hazard ratio (VERQUVO over Placebo), based on a Cox proportional hazards model.] (0.83, 0.98)
- All-cause mortality | 266 (10.5) |  | 285 (11.3)
- Heart failure hospitalization | 691 (27.4) |  | 747 (29.6)
N=Number of patients in ITT population; n=Total number of events of heart failure hospitalization, or number of patients with ≥1 event for all other rows.

16 HOW SUPPLIED/STORAGE AND HANDLING

16.1 How Supplied

VERQUVO (vericiguat) is available as round, film-coated, biconvex tablets in the following configurations:

Strength | Color | Markings (debossed) Obverse/Reverse | NDC #
Strength | Color | Markings (debossed) Obverse/Reverse | 14 Count Bottle | 30 Count Bottle | 90 Count Bottle | Carton/100 [10 blister cards of 10 tablets]
2.5 mg | White | "2.5"/"VC" | 0006-5028-01 | 0006-5028-02 | - | 0006-5028-04
5 mg | Brown-Red | "5"/"VC" | 0006-5029-01 | 0006-5029-02 | - | 0006-5029-04
10 mg | Yellow-Orange | "10"/"VC" | - | 0006-5030-01 | 0006-5030-02 | 0006-5030-04

16.2 Storage and Handling

Store at 20°C to 25°C (68°F to 77°F); excursions permitted between 15°C to 30°C (between 59°F to 86°F). See USP for Controlled Room Temperature.

17 PATIENT COUNSELING INFORMATION

Advise the patient to read the FDA-approved patient labeling (Medication Guide).

Dosing Instructions

If a dose is missed, it should be taken as soon as the patient remembers on the same day of the missed dose. Patients should not take two doses of VERQUVO on the same day.

Embryo-Fetal Toxicity
Advise pregnant women and females of reproductive potential of the potential risk to a fetus and to inform their healthcare provider of a known or suspected pregnancy. Advise females of reproductive potential to use effective contraception during treatment with VERQUVO and for one month after the final dose [see Contraindications (4), Warnings and Precautions (5.1) and Use in Specific Populations (8.1, 8.3)].

Pregnancy
Advise women who are exposed to VERQUVO during pregnancy to report their pregnancy to their healthcare provider. Health care providers should report any prenatal exposure to VERQUVO by calling 1-877-888-4231 or at https://pregnancyreporting.verquvo-us.com. [See Use in Specific Populations (8.1)].

Lactation
Advise women not to breastfeed during treatment with VERQUVO [see Use in Specific Populations (8.2)].

Manufactured for: Merck Sharp & Dohme LLC
Rahway, NJ 07065, USA

For patent information: www.msd.com/research/patent

Copyright © 2021-2026 Merck & Co., Inc., Rahway, NJ, USA, and its affiliates.
All rights reserved.

uspi-mk1242-t-2601r005

MEDICATION GUIDE
VERQUVO® (ver-KYU-voh)
(vericiguat)
tablets

What is the most important information I should know about VERQUVO?
VERQUVO may cause birth defects if taken during pregnancy.

- Females must not be pregnant when they start taking VERQUVO.
- Females who are able to get pregnant:
  - Your healthcare provider will do a pregnancy test to make sure that you are not pregnant before you start taking VERQUVO.
  - You must use effective forms of birth control during treatment and for 1 month after you stop treatment with VERQUVO. Talk to your healthcare provider about forms of birth control that you may use to prevent pregnancy during treatment with VERQUVO.
  - Tell your healthcare provider right away if you become pregnant or think you are pregnant during treatment with VERQUVO.
  - There is a Pregnancy Surveillance Program that monitors pregnancy outcomes in women exposed to VERQUVO during pregnancy. Patients should report any exposure to VERQUVO during pregnancy by calling 1-877-888-4231 or at https://pregnancyreporting.verquvo-us.com.

What is VERQUVO?
VERQUVO is a prescription medicine used in adults who are having symptoms of their chronic (long-lasting) heart failure, who have had a recent hospitalization or the need to receive intravenous (IV) medicines and have an ejection fraction (amount of blood pumped with each heartbeat) of less than 45 percent:

- to reduce the risk of dying and
- to reduce the need to be hospitalized

Heart failure happens when your heart is weak and cannot pump enough blood to your lungs and the rest of your body.
It is not known if VERQUVO is safe and effective in children.

Do not take VERQUVO if you:

- are taking another medicine called a soluble guanylate cyclase stimulator (sGC). Ask your healthcare provider if you are not sure if you are taking an sGC medicine.
- are pregnant. See “What is the most important information I should know about VERQUVO?”

Before you take VERQUVO, tell your healthcare provider about all your medical conditions, including if you:

- are breastfeeding or plan to breastfeed. It is not known if VERQUVO passes into your breast milk. Do not breastfeed if you take VERQUVO. Talk with your healthcare provider about the best way to feed your baby if you take VERQUVO.

Tell your healthcare provider about all the medicines you take, including prescription and over-the-counter medicines, vitamins, and herbal supplements. Certain other medicines may affect how VERQUVO works.

How should I take VERQUVO?

- Take VERQUVO exactly as your healthcare provider tells you to.
- Take VERQUVO 1 time each day with food.
- Swallow VERQUVO tablets whole. If you are not able to swallow the tablet whole, you may crush VERQUVO tablets and mix with water right before taking your dose.
- Your healthcare provider may change your dose — when you first start taking VERQUVO to find the best dose for you and how well you tolerate VERQUVO.
- If you miss a dose, take the missed dose as soon as you remember on the same day of the missed dose. Do not take 2 doses of VERQUVO on the same day to make up for a missed dose.
- If you take too much VERQUVO, call your healthcare provider or go to the nearest hospital emergency room right away.

What are the possible side effects of VERQUVO?
VERQUVO may cause serious side effects, including:
See “What is the most important information I should know about VERQUVO?”
The most common side effects of VERQUVO include:

- low blood pressure
- low red blood cells (anemia)

These are not all the possible side effects of VERQUVO. Call your doctor for medical advice about side effects. You may report side effects to FDA at 1-800-FDA-1088.

How should I store VERQUVO?

- Store VERQUVO at room temperature between 68°F to 77°F (20°C to 25°C).

Keep VERQUVO and all medicines out of the reach of children.
General information about the safe and effective use of VERQUVO.
Medicines are sometimes prescribed for purposes other than those listed in a Medication Guide. Do not use VERQUVO for a condition for which it was not prescribed. Do not give VERQUVO to other people, even if they have the same symptoms you have. It may harm them.
You can ask your pharmacist or healthcare provider for information about VERQUVO that is written for health professionals.

What are the ingredients in VERQUVO?
Active ingredient: vericiguat.
Inactive ingredients: croscarmellose sodium, hypromellose, lactose monohydrate, magnesium stearate, microcrystalline cellulose, sodium lauryl sulfate.
The tablet film coating contains: hypromellose, talc, titanium dioxide. The film-coating for the 5 mg tablet also contains ferric oxide red. The film-coating for the 10 mg tablet also contains ferric oxide yellow.

Manufactured for: Merck Sharp & Dohme LLC
Rahway, NJ 07065, USA
For patent information: www.msd.com/research/patent
Copyright © 2021-2023 Merck & Co., Inc., Rahway, NJ, USA, and its affiliates.
All rights reserved.
usmg-mk1242-t-2307r004

This Medication Guide has been approved by the U.S. Food and Drug Administration

Revised: 07/2023

PRINCIPAL DISPLAY PANEL - 2.5 mg Tablet Bottle Label

NDC 0006-5028-02

Verquvo ®

(vericiguat) tablets

2.5 mg

Dispense the accompanying Medication
Guide to each patient.

Each tablet contains 2.5 mg vericiguat.

Rx only

30 Tablets

PRINCIPAL DISPLAY PANEL - 5 mg Tablet Bottle Label

NDC 0006-5029-02

Verquvo ®

(vericiguat) tablets

5 mg

Dispense the accompanying Medication
Guide to each patient.

Each tablet contains 5 mg vericiguat.

Rx only

30 Tablets

PRINCIPAL DISPLAY PANEL - 10 mg Tablet Bottle Label

NDC 0006-5030-01

Verquvo ®

(vericiguat) tablets

10 mg

Dispense the accompanying Medication
Guide to each patient.

Each tablet contains 10 mg vericiguat.

Rx only

30 Tablets